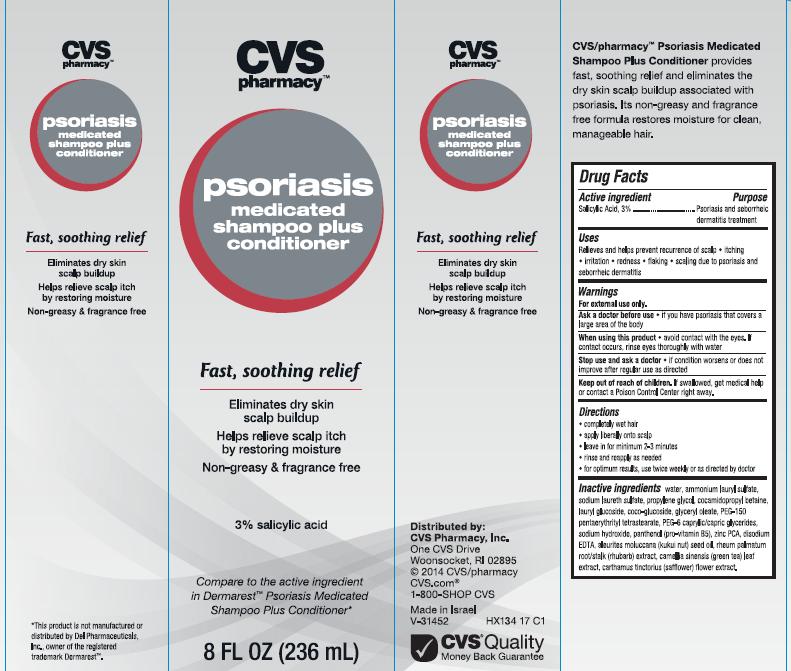 DRUG LABEL: CVS PSORIASIS MEDICATED
NDC: 59779-135 | Form: LIQUID
Manufacturer: CVS Pharmacy
Category: otc | Type: HUMAN OTC DRUG LABEL
Date: 20140923

ACTIVE INGREDIENTS: SALICYLIC ACID 3 g/100 mL
INACTIVE INGREDIENTS: WATER; AMMONIUM LAURYL SULFATE; SODIUM LAURETH-3 SULFATE; PROPYLENE GLYCOL; COCAMIDOPROPYL BETAINE; LAURYL GLUCOSIDE; COCO GLUCOSIDE; GLYCERYL OLEATE; PEG-150 PENTAERYTHRITYL TETRASTEARATE; PEG-6 CAPRYLIC/CAPRIC GLYCERIDES; SODIUM HYDROXIDE; PANTHENOL; ZINC PIDOLATE; EDETATE DISODIUM; KUKUI NUT OIL; RHEUM PALMATUM ROOT; GREEN TEA LEAF; SAFFLOWER

CVS pharmacy™ psoriasis

Active ingredient

Salicylic Acid, 3%

Purpose

Psoriasis and seborrheic dermatitis treatment

Uses

Relieves and helps prevent recurrence of scalp

- itching
- irritation
- redness
- flaking
- scaling due to psoriasis and seborrheic dermatitis

Warnings

For external use only.

Ask a doctor before use

if you have psoriasis that covers a large area of the body

When using this product

- avoid contact with the eyes. If contact occurs, rinse eyes thoroughly with water

Stop use and ask a doctor

- if condition worsens or does not improve after regular use as directed

Keep out of reach of children.

If swallowed, get medical help or contact a Poison Control Center right away.

Directions

- completely wet hair
- apply liberally onto scalp
- leave in for minimum 2-3 minutes
- rinse and reapply as needed
- for optimum results, use twice weekly or as directed by doctor

Inactive Ingredients

water, ammonium lauryl sulfate, sodium laureth sulfate, propylene glycol, cocamidopropyl betaine, lauryl glucoside, coco-glucoside, glyceryl oleate, PEG-150 pentaerythrityl tetrastearate, PEG-6 caprylic/capric glycerides, sodium hydroxide, panthenol (pro-vitamin B5), zinc PCA, disodium EDTA, aleurites moluccana (kukui nut) seed oil, rheum palmatum root/stalk (rhubarb) extract, camellia sinensis (green tea) leaf extract, carthamus tinctorius (safflower) flower extract.

Package/Label Principal Display Panel

CVS pharmacy™
psoriasis
medicated
shampoo plus
conditioner

Fast, soothing relief

Eliminates dry skin
scalp buildup

Helps relieve scalp itch
by restoring moisture

Non-greasy & fragrance free

3% salicylic acid

Compare to the active ingredient
in Dermarest™ Psoriasis Medicated
Shampoo Plus Conditioner*

8 FL OZ (236 mL)

*This product is not manufactured or distributed by Del Pharmaceuticals, Inc., owner of the registered trademark Dermarest™.

Distributed by:
CVS Pharmacy, Inc.
One CVS Drive
Woonsocket, RI 02895
© 2014 CVS/pharmacy
CVS.com®
1-800-SHOP CVS

Made in Israel
V-31452
HX134 17 C1

CVS® Quality
Money Back Guarantee

CVS/pharmacy™ Psoriasis Medicated Shampoo Plus Conditioner provides fast, soothing relief and eliminates the dry skin scalp buildup associated with psoriasis. Its non-greasy and fragrance free formula restores moisture for clean, manageable hair.

Carton Label